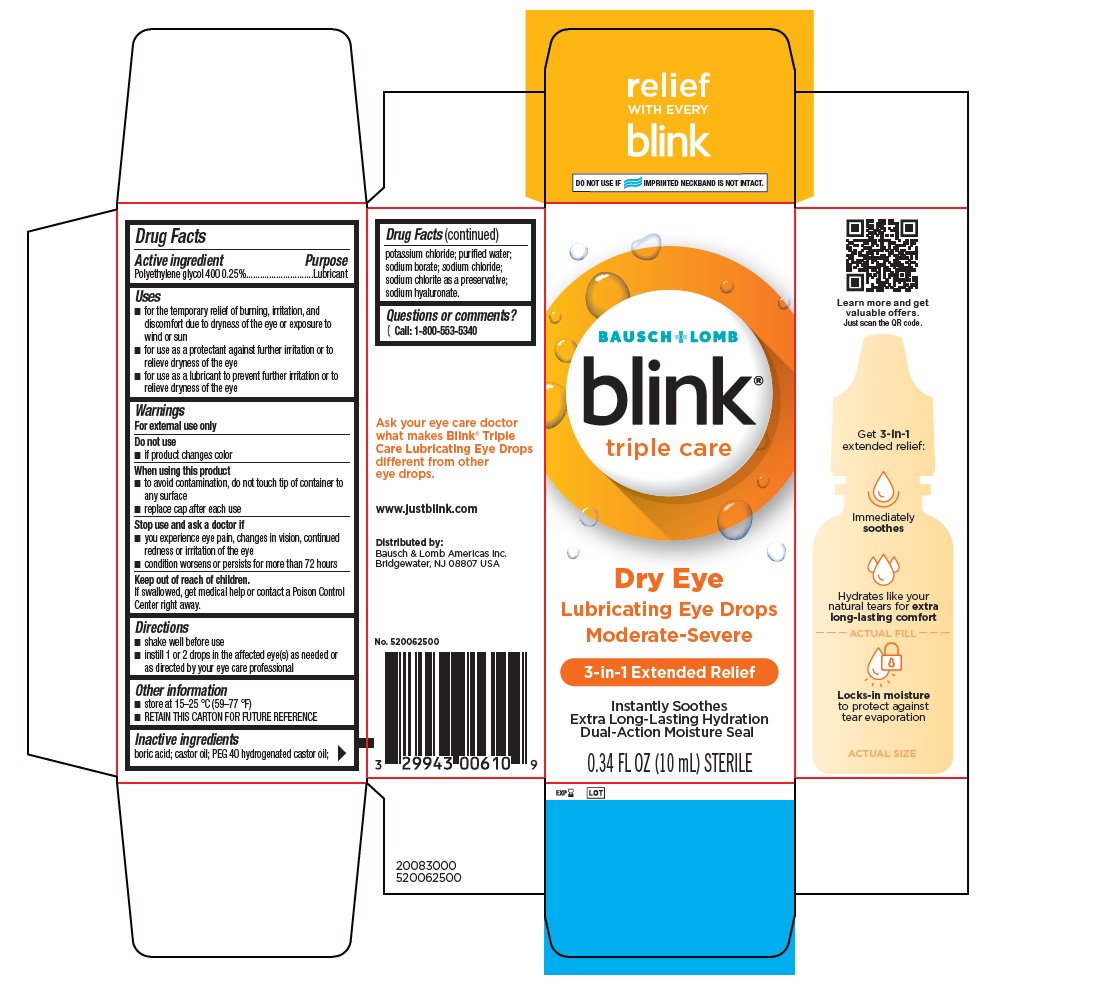 DRUG LABEL: BLINK TRIPLE CARE
NDC: 29943-006 | Form: SOLUTION/ DROPS
Manufacturer: Bausch & Lomb Incorporated
Category: otc | Type: HUMAN OTC DRUG LABEL
Date: 20260122

ACTIVE INGREDIENTS: POLYETHYLENE GLYCOL 400 2.5 mg/1 mL
INACTIVE INGREDIENTS: BORIC ACID; CASTOR OIL; POLYOXYL 40 HYDROGENATED CASTOR OIL; POTASSIUM CHLORIDE; WATER; SODIUM BORATE; SODIUM CHLORIDE; SODIUM CHLORITE; HYALURONATE SODIUM

BLINK®TRIPLE CARE

Drug Facts

Active Ingredient

Polyethylene glycol 400 0.25%

Purpose

Lubricant

Uses

- for the temporary relief of burning, irritation, and discomfort due to dryness of the eye or exposure to wind or sun
- for use as a protectant against further irritation or to relieve dryness of the eye
- for use as a lubricant to prevent further irritation or to relieve dryness of the eye.

Warnings

For external use only

Do not use

- if product changes color
  When using this product
- to avoid contamination, do not touch tip of container to any surface
- replace cap after each use

Stop use and ask a doctor if

- you experience eye pain, changes in vision, continued redness or irritation of the eye
- condition worsens or persists for more than 72 hours

Keep out of the reach of children.

If swallowed, get medical help or contact a Poison Control Center right away.

Directions

- shake well before use.
- instill 1 or 2 drops in the affected eye(s) as needed or as directed by your eye care professional.

Other Information

- Store at 15-25 °C (59-77 °F)
- RETAIN THIS CARTON FOR FUTURE REFERENCE

Inactive Ingredients

boric acid; castor oil; PEG 40 hydrogenated castor oil; potassium chloride; puriﬁed water; sodium borate; sodium chloride; sodium chlorite as a preservative; sodium hyaluronate.

Questions or comments?

[phone icon] Call: 1-800-553-5340

PRINCIPAL DISPLAY PANEL

BAUSCH + LOMB

blink®
triple care

Dry Eye
Lubricating Eye Drops
Moderate-Severe

3-in-1 Extended Relief

Instantly Soothes

Extra Long-Lasting Hydration
Dual-Action Moisture Seal

0.34 FL OZ (10 mL) STERILE